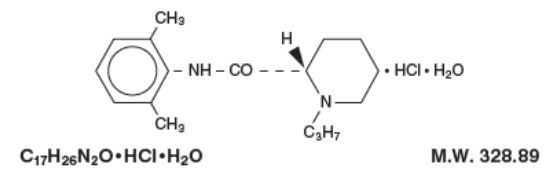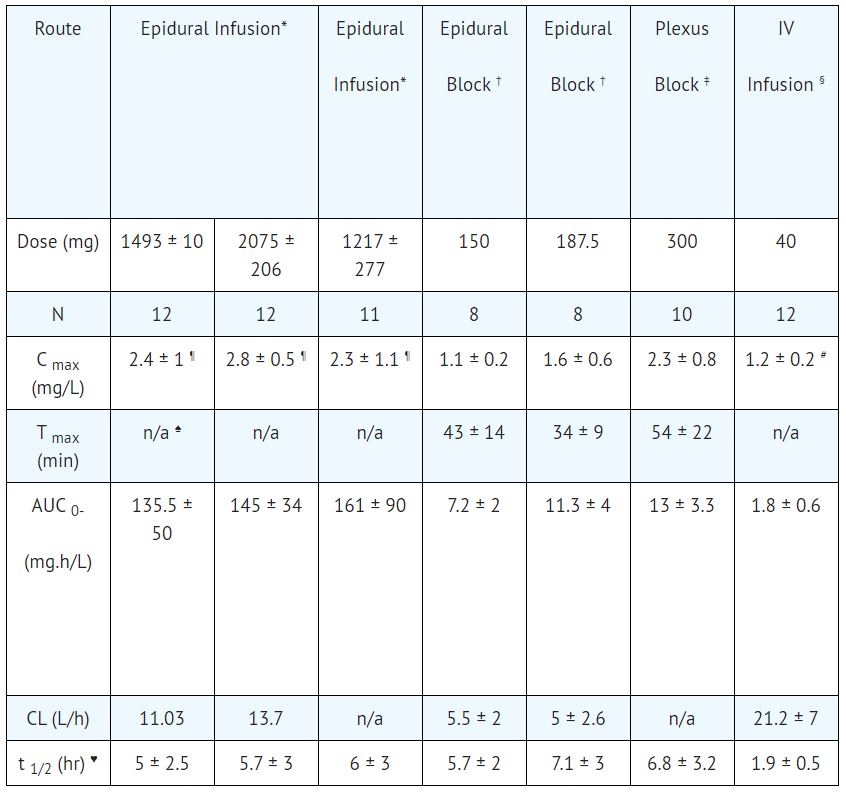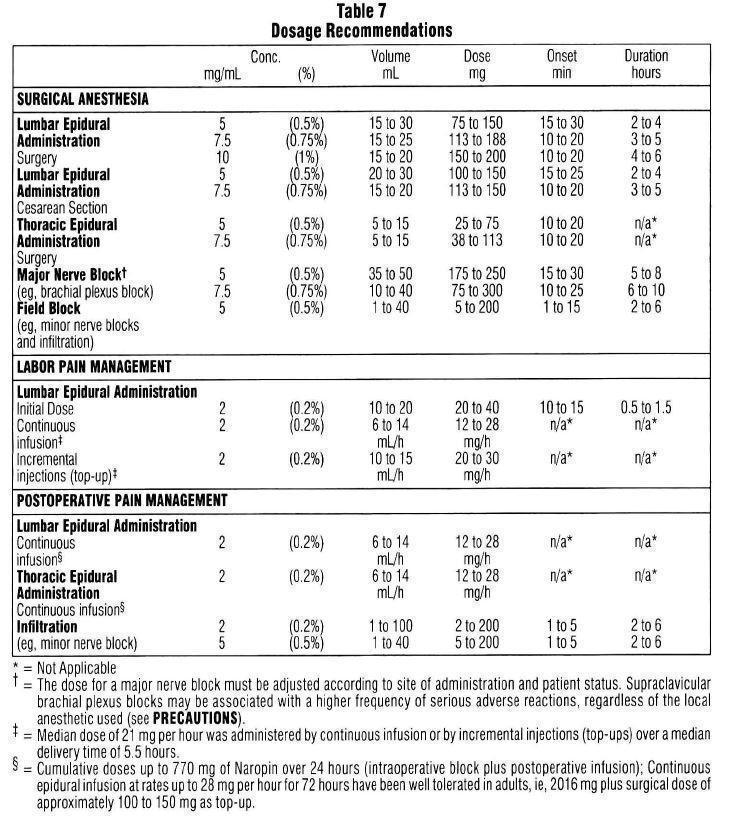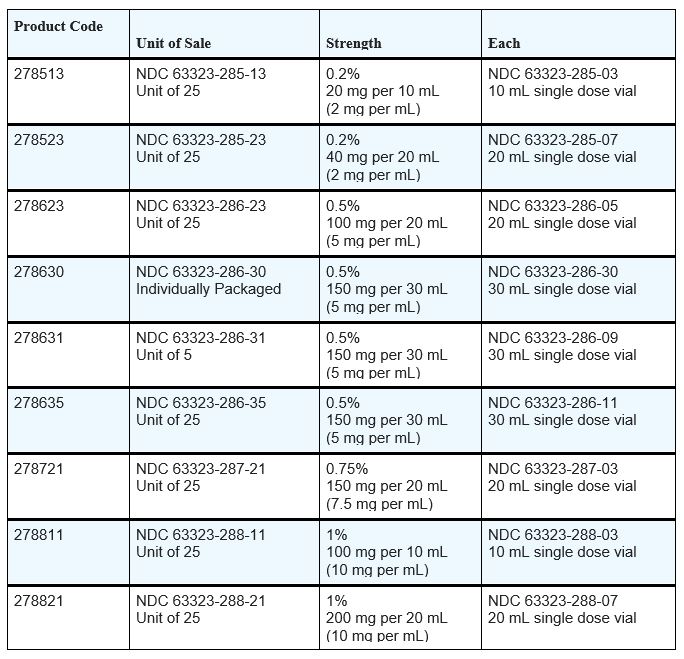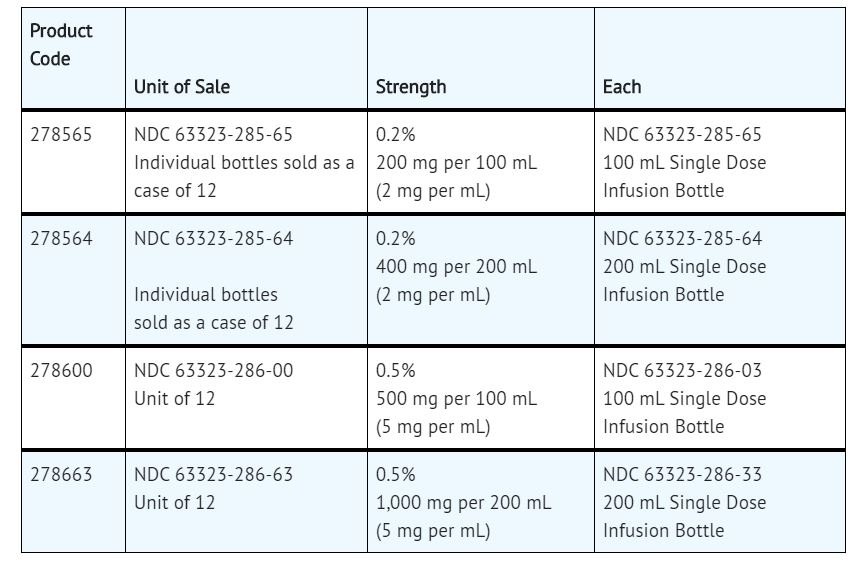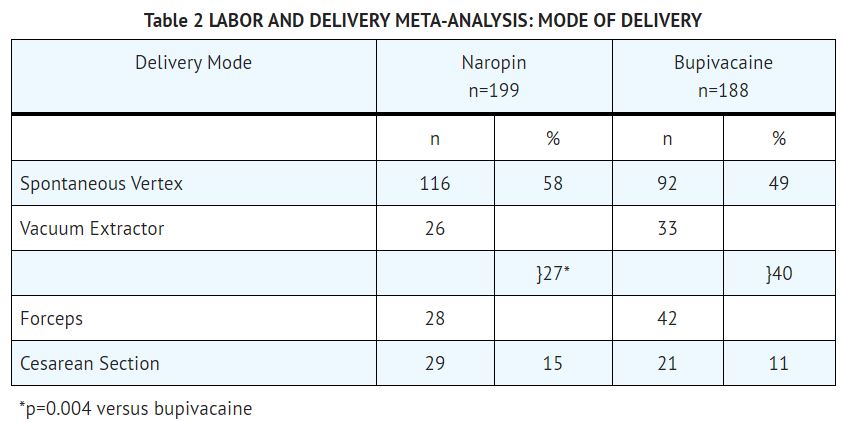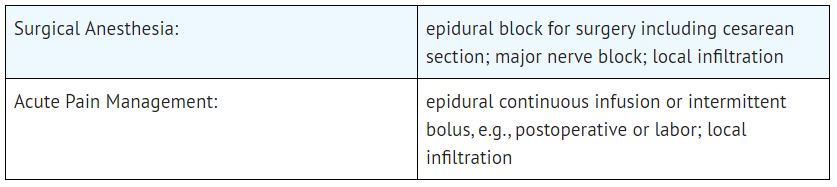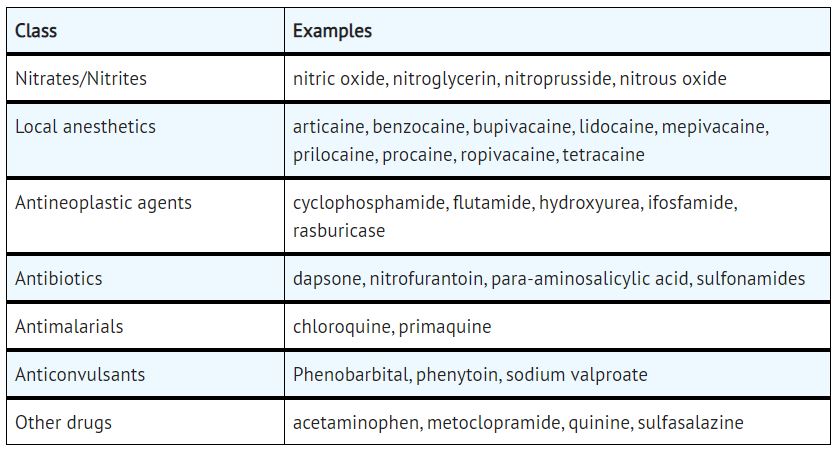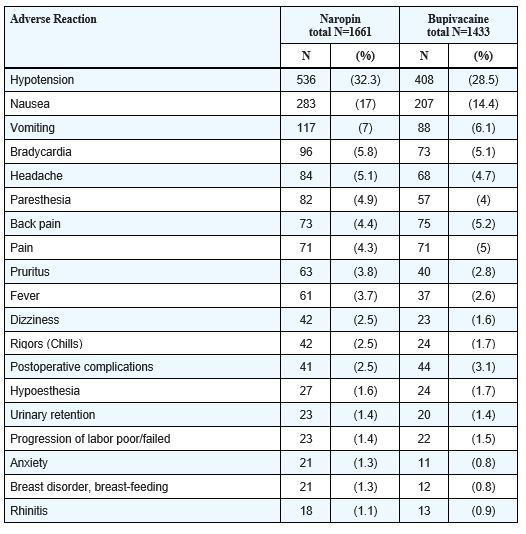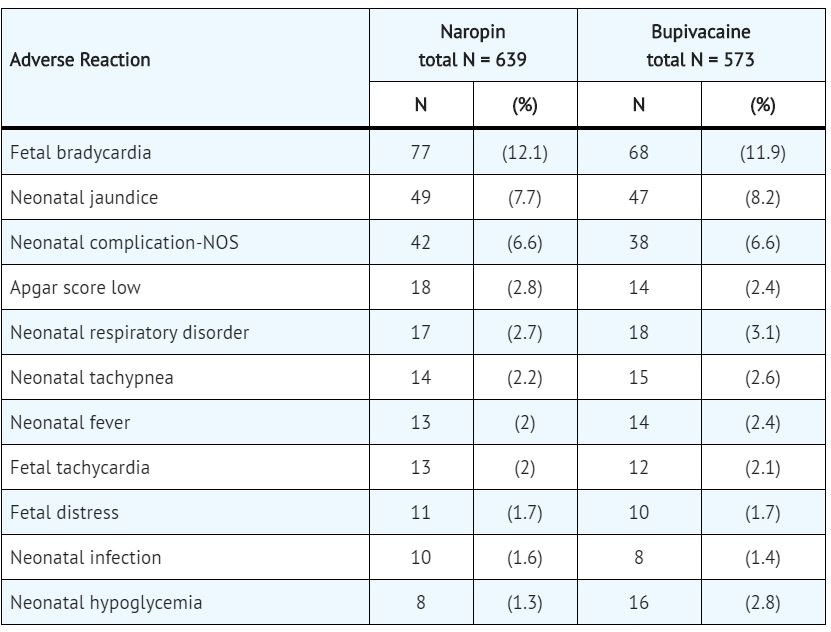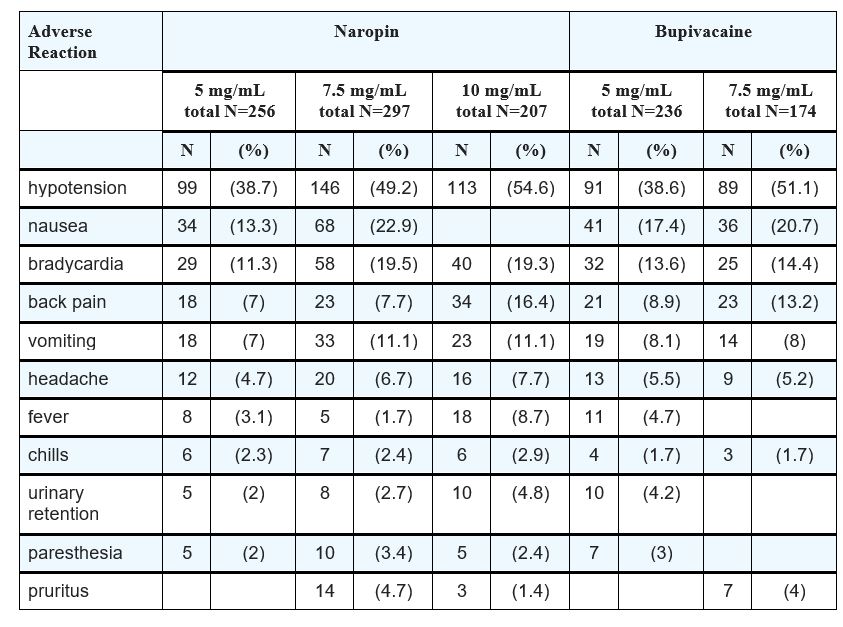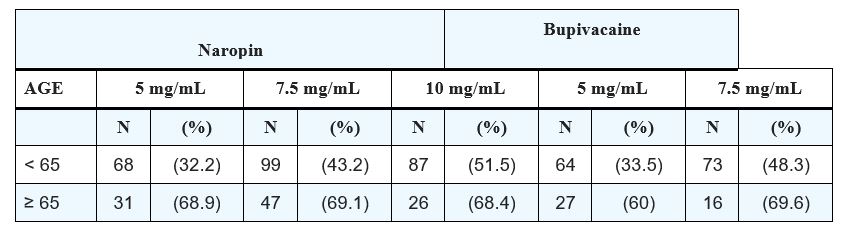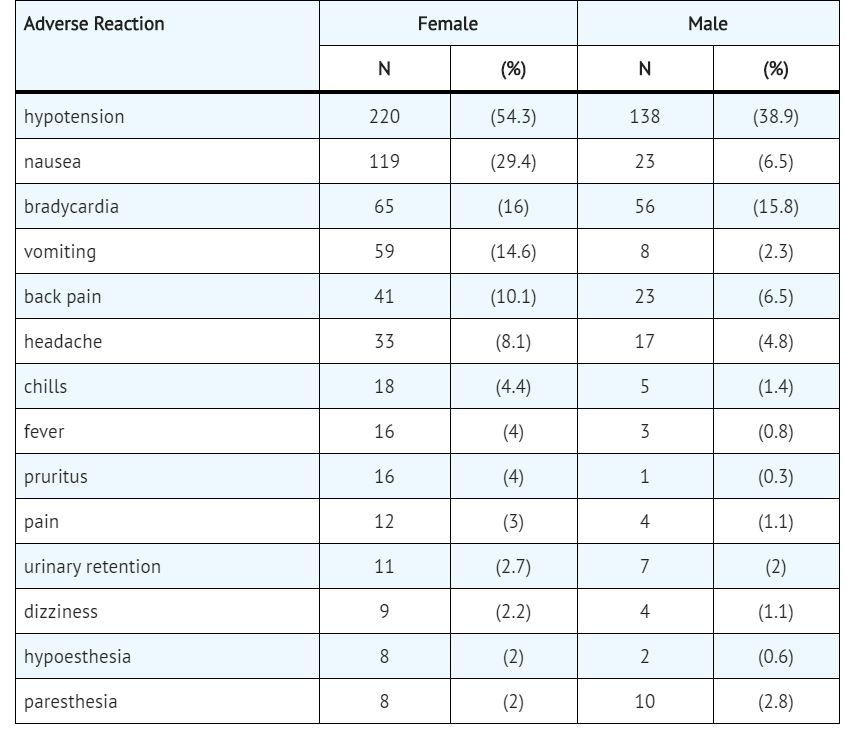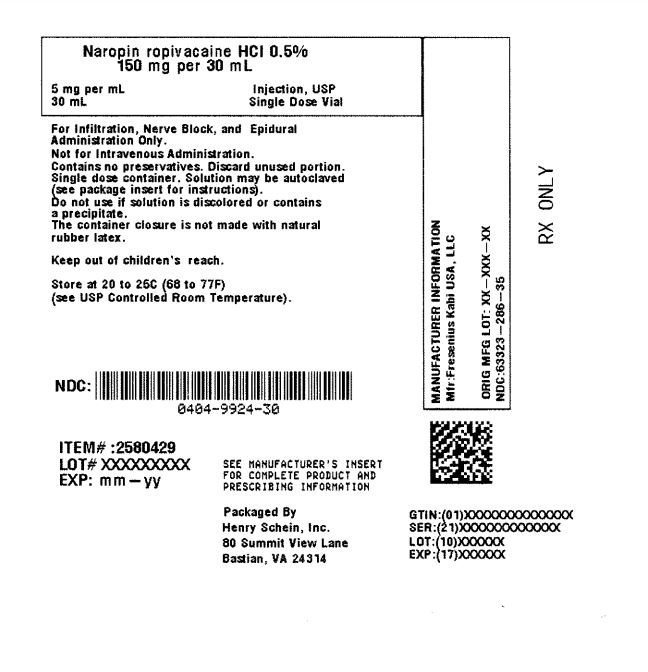 DRUG LABEL: NAROPIN
NDC: 0404-9924 | Form: INJECTION, SOLUTION
Manufacturer: Henry Schein, Inc.
Category: prescription | Type: HUMAN PRESCRIPTION DRUG LABEL
Date: 20251103

ACTIVE INGREDIENTS: ROPIVACAINE HYDROCHLORIDE 5 mg/1 mL
INACTIVE INGREDIENTS: SODIUM CHLORIDE 8 mg/1 mL; SODIUM HYDROXIDE; HYDROCHLORIC ACID

Naropin®
(ropivacaine HCl Injection, USP)
Rx only

DESCRIPTION

Naropin ® Injection contains ropivacaine HCl which is a member of the amino amide class of local anesthetics. Naropin Injection is a sterile, isotonic solution that contains the enantiomerically pure drug substance, sodium chloride for isotonicity and water for injection. Sodium hydroxide and/or hydrochloric acid may be used for pH adjustment. It is administered parenterally.
Ropivacaine HCl is chemically described as S-(-)-1-propyl-2',6'-pipecoloxylidide hydrochloride monohydrate. The drug substance is a white crystalline powder, with the following structural formula:

At 25°C ropivacaine HCl has a solubility of 53.8 mg/mL in water, a distribution ratio between n-octanol and phosphate buffer at pH 7.4 of 14:1 and a pKa of 8.07 in 0.1 M KCl solution. The pKa of ropivacaine is approximately the same as bupivacaine (8.1) and is similar to that of mepivacaine (7.7). However, ropivacaine has an intermediate degree of lipid solubility compared to bupivacaine and mepivacaine.

Naropin Injection is preservative-free and is available in single dose containers in 2 (0.2%), 5 (0.5%), 7.5 (0.75%) and 10 mg/mL (1%) concentrations. The specific gravity of Naropin Injection solutions range from 1.002 to 1.005 at 25°C.

CLINICAL PHARMACOLOGY

Mechanism of Action
Ropivacaine is a member of the amino amide class of local anesthetics and is supplied as the pure S-(-)-enantiomer. Local anesthetics block the generation and the conduction of nerve impulses, presumably by increasing the threshold for electrical excitation in the nerve, by slowing the propagation of the nerve impulse, and by reducing the rate of rise of the action potential. In general, the progression of anesthesia is related to the diameter, myelination and conduction velocity of affected nerve fibers. Clinically, the order of loss of nerve function is as follows: (1) pain, (2) temperature, (3) touch, (4) proprioception, and (5) skeletal muscle tone.
PHARMACOKINETICS:
Absorption
The systemic concentration of ropivacaine is dependent on the total dose and concentration of drug administered, the route of administration, the patient's hemodynamic/circulatory condition, and the vascularity of the administration site.
From the epidural space, ropivacaine shows complete and biphasic absorption. The half-lives of the 2 phases, (mean ± SD) are 14 ± 7 minutes and 4.2 ± 0.9 h, respectively. The slow absorption is the rate limiting factor in the elimination of ropivacaine that explains why the terminal half-life is longer after epidural than after intravenous administration. Ropivacaine shows dose-proportionality up to the highest intravenous dose studied, 80 mg, corresponding to a mean ± SD peak plasma concentration of 1.9 ± 0.3 mcg/mL.
Table 1 Pharmacokinetic (plasma concentration-time) data from clinical trials

* Continuous 72 hour epidural infusion after an epidural block with 5 or 10 mg/mL.
† Epidural anesthesia with 7.5 mg/mL (0.75%) for cesarean delivery.
‡ Brachial plexus block with 7.5 mg/mL (0.75%) ropivacaine.
§ 20 minute IV infusion to volunteers (40 mg).
¶ C max measured at the end of infusion (i.e., at 72 hr).
# C max measured at the end of infusion (i.e., at 20 minutes).
♠ n/a=not applicable
♥ t ½ is the true terminal elimination half-life. On the other hand, t ½ follows absorption dependent elimination (flip-flop) after non-intravenous administration.
In some patients after a 300 mg dose for brachial plexus block, free plasma concentrations of ropivacaine may approach the threshold for CNS toxicity (see PRECAUTIONS). At a dose of greater than 300 mg, for local infiltration, the terminal half-life may be longer (>30 hours).
Distribution
After intravascular infusion, ropivacaine has a steady-state volume of distribution of 41 ± 7 liters. Ropivacaine is 94% protein bound, mainly to α 1-acid glycoprotein. An increase in total plasma concentrations during continuous epidural infusion has been observed, related to a postoperative increase of α 1-acid glycoprotein. Variations in unbound, i.e., pharmacologically active, concentrations have been less than in total plasma concentration. Ropivacaine readily crosses the placenta and equilibrium in regard to unbound concentration will be rapidly reached (see PRECAUTIONS, LABOR AND DELIVERY).
Metabolism
Ropivacaine is extensively metabolized in the liver, predominantly by aromatic hydroxylation mediated by cytochrome P4501A to 3-hydroxy ropivacaine. After a single IV dose approximately 37% of the total dose is excreted in the urine as both free and conjugated 3-hydroxy ropivacaine. Low concentrations of 3-hydroxy ropivacaine have been found in the plasma. Urinary excretion of the 4-hydroxy ropivacaine, and both the 3-hydroxy N-de-alkylated (3-OH-PPX) and 4-hydroxy N-de-alkylated (4-OH-PPX) metabolites account for less than 3% of the dose. An additional metabolite, 2-hydroxy-methyl-ropivacaine, has been identified but not quantified in the urine. The N-de-alkylated metabolite of ropivacaine (PPX) and 3-OH-ropivacaine are the major metabolites excreted in the urine during epidural infusion. Total PPX concentration in the plasma was about half as that of total ropivacaine; however, mean unbound concentrations of PPX were about 7 to 9 times higher than that of unbound ropivacaine following continuous epidural infusion up to 72 hours. Unbound PPX, 3-hydroxy and 4-hydroxy ropivacaine, have a pharmacological activity in animal models less than that of ropivacaine. There is no evidence of in vivo racemization in urine of ropivacaine.
Elimination
The kidney is the main excretory organ for most local anesthetic metabolites. In total, 86% of the ropivacaine dose is excreted in the urine after intravenous administration of which only 1% relates to unchanged drug. After intravenous administration ropivacaine has a mean ± SD total plasma clearance of 387 ± 107 mL/min, an unbound plasma clearance of 7.2 ± 1.6 L/min, and a renal clearance of 1 mL/min. The mean ± SD terminal half-life is 1.8 ± 0.7 h after intravascular administration and 4.2 ± 1 h after epidural administration (see ABSORPTION).
Pharmacodynamics
Studies in humans have demonstrated that, unlike most other local anesthetics, the presence of epinephrine has no major effect on either the time of onset or the duration of action of ropivacaine. Likewise, addition of epinephrine to ropivacaine has no effect on limiting systemic absorption of ropivacaine.
Systemic absorption of local anesthetics can produce effects on the central nervous and cardiovascular systems. At blood concentrations achieved with therapeutic doses, changes in cardiac conduction, excitability, refractoriness, contractility, and peripheral vascular resistance have been reported. Toxic blood concentrations depress cardiac conduction and excitability, which may lead to atrioventricular block, ventricular arrhythmias and to cardiac arrest, sometimes resulting in fatalities. In addition, myocardial contractility is depressed and peripheral vasodilation occurs, leading to decreased cardiac output and arterial blood pressure.
Following systemic absorption, local anesthetics can produce central nervous system stimulation, depression or both. Apparent central stimulation is usually manifested as restlessness, tremors and shivering, progressing to convulsions, followed by depression and coma, progressing ultimately to respiratory arrest. However, the local anesthetics have a primary depressant effect on the medulla and on higher centers. The depressed stage may occur without a prior excited stage.
In 2 clinical pharmacology studies (total n=24) ropivacaine and bupivacaine were infused (10 mg/min) in human volunteers until the appearance of CNS symptoms, e.g., visual or hearing disturbances, perioral numbness, tingling and others. Similar symptoms were seen with both drugs. In 1 study, the mean ± SD maximum tolerated intravenous dose of ropivacaine infused (124 ± 38 mg) was significantly higher than that of bupivacaine (99 ± 30 mg) while in the other study the doses were not different (115 ± 29 mg of ropivacaine and 103 ± 30 mg of bupivacaine). In the latter study, the number of subjects reporting each symptom was similar for both drugs with the exception of muscle twitching which was reported by more subjects with bupivacaine than ropivacaine at comparable intravenous doses. At the end of the infusion, ropivacaine in both studies caused significantly less depression of cardiac conductivity (less QRS widening) than bupivacaine. Ropivacaine and bupivacaine caused evidence of depression of cardiac contractility, but there were no changes in cardiac output.
Clinical data in one published article indicate that differences in various pharmacodynamic measures were observed with increasing age. In one study, the upper level of analgesia increased with age, the maximum decrease of mean arterial pressure (MAP) declined with age during the first hour after epidural administration, and the intensity of motor blockade increased with age. However, no pharmacokinetic differences were observed between elderly and younger patients.
In non-clinical pharmacology studies comparing ropivacaine and bupivacaine in several animal species, the cardiac toxicity of ropivacaine was less than that of bupivacaine, although both were considerably more toxic than lidocaine. Arrhythmogenic and cardio-depressant effects were seen in animals at significantly higher doses of ropivacaine than bupivacaine. The incidence of successful resuscitation was not significantly different between the ropivacaine and bupivacaine groups.
Clinical Trials
Ropivacaine was studied as a local anesthetic both for surgical anesthesia and for acute pain management (see DOSAGE AND ADMINISTRATION).
The onset, depth and duration of sensory block are, in general, similar to bupivacaine. However, the depth and duration of motor block, in general, are less than that with bupivacaine.
Epidural Administration In Surgery
There were 25 clinical studies performed in 900 patients to evaluate Naropin epidural injection for general surgery. Naropin was used in doses ranging from 75 to 250 mg. In doses of 100 to 200 mg, the median (1st to 3rd quartile) onset time to achieve a T10 sensory block was 10 (5 to 13) minutes and the median (1st to 3rd quartile) duration at the T10 level was 4 (3 to 5) hours (see DOSAGE AND ADMINISTRATION). Higher doses produced a more profound block with a greater duration of effect.
Epidural Administration In Cesarean Section
A total of 12 studies were performed with epidural administration of Naropin for cesarean section. Eight of these studies involved 218 patients using the concentration of 5 mg/mL (0.5%) in doses up to 150 mg. Median onset measured at T6 ranged from 11 to 26 minutes. Median duration of sensory block at T6 ranged from 1.7 to 3.2 h, and duration of motor block ranged from 1.4 to 2.9 h. Naropin provided adequate muscle relaxation for surgery in all cases.
In addition, 4 active controlled studies for cesarean section were performed in 264 patients at a concentration of 7.5 mg/mL (0.75%) in doses up to 187.5 mg. Median onset measured at T6 ranged from 4 to 15 minutes. Seventy-seven to 96% of Naropin-exposed patients reported no pain at delivery. Some patients received other anesthetic, analgesic, or sedative modalities during the course of the operative procedure.
Epidural Administration In Labor And Delivery
A total of 9 double-blind clinical studies, involving 240 patients were performed to evaluate Naropin for epidural block for management of labor pain. When administered in doses up to 278 mg as intermittent injections or as a continuous infusion, Naropin produced adequate pain relief.
A prospective meta-analysis on 6 of these studies provided detailed evaluation of the delivered newborns and showed no difference in clinical outcomes compared to bupivacaine. There were significantly fewer instrumental deliveries in mothers receiving ropivacaine as compared to bupivacaine. Epidural Administration In Postoperative Pain Management

There were 8 clinical studies performed in 382 patients to evaluate Naropin 2 mg/mL (0.2%) for postoperative pain management after upper and lower abdominal surgery and after orthopedic surgery. The studies utilized intravascular morphine via PCA as a rescue medication and quantified as an efficacy variable.

Epidural anesthesia with Naropin 5 mg/mL, (0.5%) was used intraoperatively for each of these procedures prior to initiation of postoperative Naropin. The incidence and intensity of the motor block were dependent on the dose rate of Naropin and the site of injection. Cumulative doses of up to 770 mg of ropivacaine were administered over 24 hours (intraoperative block plus postoperative continuous infusion). The overall quality of pain relief, as judged by the patients, in the ropivacaine groups was rated as good or excellent (73% to 100%). The frequency of motor block was greatest at 4 hours and decreased during the infusion period in all groups. At least 80% of patients in the upper and lower abdominal studies and 42% in the orthopedic studies had no motor block at the end of the 21-hour infusion period. Sensory block was also dose rate-dependent and a decrease in spread was observed during the infusion period.
A double-blind, randomized, clinical trial compared lumbar epidural infusion of Naropin (n=26) and bupivacaine (n=26) at 2 mg/mL (8 mL/h), for 24 hours after knee replacement. In this study, the pain scores were higher in the Naropin group, but the incidence and the intensity of motor block were lower.
Continuous epidural infusion of Naropin 2 mg/mL (0.2%) during up to 72 hours for postoperative pain management after major abdominal surgery was studied in 2 multicenter, double-blind studies. A total of 391 patients received a low thoracic epidural catheter, and Naropin 7.5 mg/L (0.75%) was given for surgery, in combination with GA. Postoperatively, Naropin 2 mg/mL (0.2%), 4 to 14 mL/h, alone or with fentanyl 1, 2, or 4 mcg/mL was infused through the epidural catheter and adjusted according to the patient's needs. These studies support the use of Naropin 2 mg/mL (0.2%) for epidural infusion at 6 to 14 mL/h (12 to 28 mg) for up to 72 hours and demonstrated adequate analgesia with only slight and nonprogressive motor block in cases of moderate to severe postoperative pain.
Clinical studies with 2 mg/mL (0.2%) Naropin have demonstrated that infusion rates of 6 to 14 mL (12 to 28 mg) per hour provide adequate analgesia with nonprogressive motor block in cases of moderate to severe postoperative pain. In these studies, this technique resulted in a significant reduction in patients' morphine rescue dose requirement. Clinical experience supports the use of Naropin epidural infusions for up to 72 hours.
Peripheral Nerve Block
Naropin, 5 mg/mL (0.5%), was evaluated for its ability to provide anesthesia for surgery using the techniques of Peripheral Nerve Block. There were 13 studies performed including a series of 4 pharmacodynamic and pharmacokinetic studies performed on minor nerve blocks. From these, 235 Naropin-treated patients were evaluable for efficacy. Naropin was used in doses up to 275 mg. When used for brachial plexus block, onset depended on technique used. Supraclavicular blocks were consistently more successful than axillary blocks. The median onset of sensory block (anesthesia) produced by ropivacaine 0.5% via axillary block ranged from 10 minutes (medial brachial cutaneous nerve) to 45 minutes (musculocutaneous nerve). Median duration ranged from 3.7 hours (medial brachial cutaneous nerve) to 8.7 hours (ulnar nerve). The 5 mg/mL (0.5%) Naropin solution gave success rates from 56% to 86% for axillary blocks, compared with 92% for supraclavicular blocks.
In addition, Naropin, 7.5 mg/mL (0.75%), was evaluated in 99 Naropin-treated patients, in 2 double-blind studies, performed to provide anesthesia for surgery using the techniques of Brachial Plexus Block. Naropin 7.5 mg/mL was compared to bupivacaine 5 mg/mL. In 1 study, patients underwent axillary brachial plexus block using injections of 40 mL (300 mg) of Naropin, 7.5 mg/mL (0.75%) or 40 mL injections of bupivacaine, 5 mg/mL (200 mg). In a second study, patients underwent subclavian perivascular brachial plexus block using 30 mL (225 mg) of Naropin, 7.5 mg/mL (0.75%) or 30 mL of bupivacaine 5 mg/mL (150 mg). There was no significant difference between the Naropin and bupivacaine groups in either study with regard to onset of anesthesia, duration of sensory blockade, or duration of anesthesia.
The median duration of anesthesia varied between 11.4 and 14.4 hours with both techniques. In one study, using the axillary technique, the quality of analgesia and muscle relaxation in the Naropin group was judged to be significantly superior to bupivacaine by both investigator and surgeon. However, using the subclavian perivascular technique, no statistically significant difference was found in the quality of analgesia and muscle relaxation as judged by both the investigator and surgeon. The use of Naropin 7.5 mg/mL for block of the brachial plexus via either the subclavian perivascular approach using 30 mL (225 mg) or via the axillary approach using 40 mL (300 mg) both provided effective and reliable anesthesia.
Local Infiltration
A total of 7 clinical studies were performed to evaluate the local infiltration of Naropin to produce anesthesia for surgery and analgesia in postoperative pain management. In these studies 297 patients who received Naropin in doses up to 200 mg (concentrations up to 5 mg/mL, 0.5%) were evaluable for efficacy. With infiltration of 100 to 200 mg Naropin, the time to first request for analgesic was 2 to 6 hours. When compared to placebo, Naropin produced lower pain scores and a reduction of analgesic consumption.

INDICATIONS AND USAGE:

Naropin is indicated for the production of local or regional anesthesia for surgery and for acute pain management.

Contraindications

Naropin is contraindicated in patients with a known hypersensitivity to ropivacaine or to any local anesthetic agent of the amide type.

Warnings

In performing Naropin blocks, unintended intravenous injection is possible and may result in cardiac arrhythmia or cardiac arrest. The potential for successful resuscitation has not been studied in humans. There have been rare reports of cardiac arrest during the use of Naropin for epidural anesthesia or peripheral nerve blockade, the majority of which occurred after unintentional accidental intravascular administration in elderly patients and in patients with concomitant heart disease. In some instances, resuscitation has been difficult. Should cardiac arrest occur, prolonged resuscitative efforts may be required to improve the probability of a successful outcome.

Naropin should be administered in incremental doses. It is not recommended for emergency situations, where a fast onset of surgical anesthesia is necessary. Historically, pregnant patients were reported to have a high risk for cardiac arrhythmias, cardiac/circulatory arrest and death when 0.75% bupivacaine (another member of the amino amide class of local anesthetics) was inadvertently rapidly injected intravenously.

Prior to receiving major blocks the general condition of the patient should be optimized and the patient should have an IV line inserted. All necessary precautions should be taken to avoid intravascular injection. Local anesthetics should only be administered by clinicians who are well versed in the diagnosis and management of dose-related toxicity and other acute emergencies which might arise from the block to be employed, and then only after insuring the immediate (without delay) availability of oxygen, other resuscitative drugs, cardiopulmonary resuscitative equipment, and the personnel resources needed for proper management of toxic reactions and related emergencies (see also ADVERSE REACTIONS, PRECAUTIONS and MANAGEMENT OF LOCAL ANESTHETIC EMERGENCIES). Delay in proper management of dose-related toxicity, underventilation from any cause, and/or altered sensitivity may lead to the development of acidosis, cardiac arrest and, possibly, death. Solutions of Naropin should not be used for the production of obstetrical paracervical block anesthesia, retrobulbar block, or spinal anesthesia (subarachnoid block) due to insufficient data to support such use. Intravenous regional anesthesia (bier block) should not be performed due to a lack of clinical experience and the risk of attaining toxic blood levels of ropivacaine.

Intra-articular infusions of local anesthetics following arthroscopic and other surgical procedures is an unapproved use, and there have been post-marketing reports of chondrolysis in patients receiving such infusions. The majority of reported cases of chondrolysis have involved the shoulder joint; cases of gleno-humeral chondrolysis have been described in pediatric and adult patients following intra-articular infusions of local anesthetics with and without epinephrine for periods of 48 to 72 hours. There is insufficient information to determine whether shorter infusion periods are not associated with these findings. The time of onset of symptoms, such as joint pain, stiffness and loss of motion can be variable, but may begin as early as the 2 nd month after surgery. Currently, there is no effective treatment for chondrolysis; patients who experienced chondrolysis have required additional diagnostic and therapeutic procedures and some required arthroplasty or shoulder replacement.

It is essential that aspiration for blood, or cerebrospinal fluid (where applicable), be done prior to injecting any local anesthetic, both the original dose and all subsequent doses, to avoid intravascular or subarachnoid injection. However, a negative aspiration does not ensure against an intravascular or subarachnoid injection.

A well-known risk of epidural anesthesia may be an unintentional subarachnoid injection of local anesthetic. Two clinical studies have been performed to verify the safety of Naropin at a volume of 3 mL injected into the subarachnoid space since this dose represents an incremental epidural volume that could be unintentionally injected. The 15 and 22.5 mg doses injected resulted in sensory levels as high as T5 and T4, respectively. Anesthesia to pinprick started in the sacral dermatomes in 2 to 3 minutes, extended to the T10 level in 10 to 13 minutes and lasted for approximately 2 hours. The results of these two clinical studies showed that a 3 mL dose did not produce any serious adverse events when spinal anesthesia blockade was achieved.

Naropin should be used with caution in patients receiving other local anesthetics or agents structurally related to amide-type local anesthetics, since the toxic effects of these drugs are additive.

Patients treated with class III antiarrhythmic drugs (e.g., amiodarone) should be under close surveillance and ECG monitoring considered, since cardiac effects may be additive.

Methemoglobinemia
Cases of methemoglobinemia have been reported in association with local anesthetic use. Although all patients are at risk for methemoglobinemia, patients with glucose-6-phosphate dehydrogenase deficiency, congenital or idiopathic methemoglobinemia, cardiac or pulmonary compromise, infants under 6 months of age, and concurrent exposure to oxidizing agents or their metabolites are more susceptible to developing clinical manifestations of the condition. If local anesthetics must be used in these patients, close monitoring for symptoms and signs of methemoglobinemia is recommended.

Signs of methemoglobinemia may occur immediately or may be delayed some hours after exposure, and are characterized by a cyanotic skin discoloration and/or abnormal coloration of the blood. Methemoglobin levels may continue to rise; therefore, immediate treatment is required to avert more serious central nervous system and cardiovascular adverse effects, including seizures, coma, arrhythmias, and death. Discontinue Naropin and any other oxidizing agents. Depending on the severity of the signs and symptoms, patients may respond to supportive care, i.e., oxygen therapy, hydration. A more severe clinical presentation may require treatment with methylene blue, exchange transfusion, or hyperbaric oxygen.

Precautions

General
The safe and effective use of local anesthetics depends on proper dosage, correct technique, adequate precautions and readiness for emergencies.
Resuscitative equipment, oxygen and other resuscitative drugs should be available for immediate use (see WARNINGS and ADVERSE REACTIONS). The lowest dosage that results in effective anesthesia should be used to avoid high plasma levels and serious adverse events. Injections should be made slowly and incrementally, with frequent aspirations before and during the injection to avoid intravascular injection. When a continuous catheter technique is used, syringe aspirations should also be performed before and during each supplemental injection. During the administration of epidural anesthesia, it is recommended that a test dose of a local anesthetic with a fast onset be administered initially and that the patient be monitored for central nervous system and cardiovascular toxicity, as well as for signs of unintended intrathecal administration before proceeding. When clinical conditions permit, consideration should be given to employing local anesthetic solutions, which contain epinephrine for the test dose because circulatory changes compatible with epinephrine may also serve as a warning sign of unintended intravascular injection. An intravascular injection is still possible even if aspirations for blood are negative. Administration of higher than recommended doses of Naropin to achieve greater motor blockade or increased duration of sensory blockade may result in cardiovascular depression, particularly in the event of inadvertent intravascular injection. Tolerance to elevated blood levels varies with the physical condition of the patient. Debilitated, elderly patients and acutely ill patients should be given reduced doses commensurate with their age and physical condition. Local anesthetics should also be used with caution in patients with hypotension, hypovolemia or heart block.
Careful and constant monitoring of cardiovascular and respiratory vital signs (adequacy of ventilation) and the patient's state of consciousness should be performed after each local anesthetic injection. It should be kept in mind at such times that restlessness, anxiety, incoherent speech, light-headedness, numbness and tingling of the mouth and lips, metallic taste, tinnitus, dizziness, blurred vision, tremors, twitching, depression, or drowsiness may be early warning signs of central nervous system toxicity. Because amide-type local anesthetics such as ropivacaine are metabolized by the liver, these drugs, especially repeat doses, should be used cautiously in patients with hepatic disease. Patients with severe hepatic disease, because of their inability to metabolize local anesthetics normally, are at a greater risk of developing toxic plasma concentrations. Local anesthetics should also be used with caution in patients with impaired cardiovascular function because they may be less able to compensate for functional changes associated with the prolongation of A-V conduction produced by these drugs.
Many drugs used during the conduct of anesthesia are considered potential triggering agents for malignant hyperthermia (MH). Amide-type local anesthetics are not known to trigger this reaction. However, since the need for supplemental general anesthesia cannot be predicted in advance, it is suggested that a standard protocol for MH management should be available.
Epidural Anesthesia
During epidural administration, Naropin should be administered in incremental doses of 3 to 5 mL with sufficient time between doses to detect toxic manifestations of unintentional intravascular or intrathecal injection. Syringe aspirations should also be performed before and during each supplemental injection in continuous (intermittent) catheter techniques. An intravascular injection is still possible even if aspirations for blood are negative. During the administration of epidural anesthesia, it is recommended that a test dose be administered initially and the effects monitored before the full dose is given. When clinical conditions permit, the test dose should contain an appropriate dose of epinephrine to serve as a warning of unintentional intravascular injection. If injected into a blood vessel, this amount of epinephrine is likely to produce a transient "epinephrine response" within 45 seconds, consisting of an increase in heart rate and systolic blood pressure, circumoral pallor, palpitations and nervousness in the unsedated patient. The sedated patient may exhibit only a pulse rate increase of 20 or more beats per minute for 15 or more seconds. Therefore, following the test dose, the heart should be continuously monitored for a heart rate increase. Patients on beta-blockers may not manifest changes in heart rate, but blood pressure monitoring can detect a rise in systolic blood pressure. A test dose of a short-acting amide anesthetic such as lidocaine is recommended to detect an unintentional intrathecal administration. This will be manifested within a few minutes by signs of spinal block (e.g., decreased sensation of the buttocks, paresis of the legs, or, in the sedated patient, absent knee jerk). An intravascular or subarachnoid injection is still possible even if results of the test dose are negative. The test dose itself may produce a systemic toxic reaction, high spinal or epinephrine-induced cardiovascular effects.
Use in Brachial Plexus Block
Ropivacaine plasma concentrations may approach the threshold for central nervous system toxicity after the administration of 300 mg of ropivacaine for brachial plexus block. Caution should be exercised when using the 300 mg dose (see OVERDOSAGE).
The dose for a major nerve block must be adjusted according to the site of administration and patient status. Supraclavicular brachial plexus blocks may be associated with a higher frequency of serious adverse reactions, regardless of the local anesthetic used.
Use in Peripheral Nerve Block
Major peripheral nerve blocks may result in the administration of a large volume of local anesthetic in highly vascularized areas, often close to large vessels where there is an increased risk of intravascular injection and/or rapid systemic absorption, which can lead to high plasma concentrations.
Use in Head and Neck Area
Small doses of local anesthetics injected into the head and neck area may produce adverse reactions similar to systemic toxicity seen with unintentional intravascular injections of larger doses. The injection procedures require the utmost care. Confusion, convulsions, respiratory depression, and/or respiratory arrest, and cardiovascular stimulation or depression have been reported. These reactions may be due to intra-arterial injection of the local anesthetic with retrograde flow to the cerebral circulation. Patients receiving these blocks should have their circulation and respiration monitored and be constantly observed. Resuscitative equipment and personnel for treating adverse reactions should be immediately available. Dosage recommendations should not be exceeded (see DOSAGE AND ADMINISTRATION).
Use in Ophthalmic Surgery
The use of Naropin in retrobulbar blocks for ophthalmic surgery has not been studied. Until appropriate experience is gained, the use of Naropin for such surgery is not recommended.
Information for Patients
When appropriate, patients should be informed in advance that they may experience temporary loss of sensation and motor activity in the anesthetized part of the body following proper administration of lumbar epidural anesthesia. Also, when appropriate, the physician should discuss other information including adverse reactions in the Naropin package insert.
Inform patients that use of local anesthetics may cause methemoglobinemia, a serious condition that must be treated promptly. Advise patients or caregivers to seek immediate medical attention if they or someone in their care experience the following signs or symptoms: pale, gray, or blue colored skin (cyanosis); headache; rapid heart rate; shortness of breath; lightheadedness; or fatigue.
Drug Interactions
Specific trials studying the interaction between ropivacaine and class III antiarrhythmic drugs (e.g., amiodarone) have not been performed, but caution is advised (see WARNINGS).
Naropin should be used with caution in patients receiving other local anesthetics or agents structurally related to amide-type local anesthetics, since the toxic effects of these drugs are additive. Cytochrome P4501A2 is involved in the formation of 3-hydroxy ropivacaine, the major metabolite. In vivo, the plasma clearance of ropivacaine was reduced by 70% during coadministration of fluvoxamine (25 mg bid for 2 days), a selective and potent CYP1A2 inhibitor. Thus strong inhibitors of cytochrome P4501A2, such as fluvoxamine, given concomitantly during administration of Naropin, can interact with Naropin leading to increased ropivacaine plasma levels. Caution should be exercised when CYP1A2 inhibitors are coadministered. Possible interactions with drugs known to be metabolized by CYP1A2 via competitive inhibition such as theophylline and imipramine may also occur. Coadministration of a selective and potent inhibitor of CYP3A4, ketoconazole (100 mg bid for 2 days with ropivacaine infusion administered 1 hour after ketoconazole) caused a 15% reduction in in vivo plasma clearance of ropivacaine.
Patients who are administered local anesthetics are at increased risk of developing methemoglobinemia when concurrently exposed to the following drugs, which could include other local anesthetics:
Examples of Drugs Associated with Methemoglobinemia:

Carcinogenesis, Mutagenesis, Impairment of Fertility
Long-term studies in animals of most local anesthetics, including ropivacaine, to evaluate the carcinogenic potential have not been conducted.
Weak mutagenic activity was seen in the mouse lymphoma test. Mutagenicity was not noted in the other assays, demonstrating that the weak signs of in vitro activity in the mouse lymphoma test were not manifest under diverse in vivo conditions.
Studies performed with ropivacaine in rats did not demonstrate an effect on fertility or general reproductive performance over 2 generations.
Pregnancy Category B
Reproduction toxicity studies have been performed in pregnant New Zealand white rabbits and Sprague-Dawley rats. During gestation days 6 to 18, rabbits received 1.3, 4.2, or 13 mg/kg/day subcutaneously. In rats, subcutaneous doses of 5.3, 11 and 26 mg/kg/day were administered during gestation days 6 to 15. No teratogenic effects were observed in rats and rabbits at the highest doses tested. The highest doses of 13 mg/kg/day (rabbits) and 26 mg/kg/day (rats) are approximately 1/3 of the maximum recommended human dose (epidural, 770 mg/24 hours) based on a mg/m 2 basis. In 2 prenatal and postnatal studies, the female rats were dosed daily from day 15 of gestation to day 20 postpartum. The doses were 5.3, 11 and 26 mg/kg/day subcutaneously. There were no treatment-related effects on late fetal development, parturition, lactation, neonatal viability, or growth of the offspring.
In another study with rats, the males were dosed daily for 9 weeks before mating and during mating. The females were dosed daily for 2 weeks before mating and then during the mating, pregnancy, and lactation, up to day 42 post coitus. At 23 mg/kg/day, an increased loss of pups was observed during the first 3 days postpartum. The effect was considered secondary to impaired maternal care due to maternal toxicity.
There are no adequate or well-controlled studies in pregnant women of the effects of Naropin on the developing fetus. Naropin should only be used during pregnancy if the benefits outweigh the risk.
Teratogenicity studies in rats and rabbits did not show evidence of any adverse effects on organogenesis or early fetal development in rats (26 mg/kg sc) or rabbits (13 mg/kg). The doses used were approximately equal to total daily dose based on body surface area. There were no treatment-related effects on late fetal development, parturition, lactation, neonatal viability, or growth of the offspring in 2 perinatal and postnatal studies in rats, at dose levels equivalent to the maximum recommended human dose based on body surface area. In another study at 23 mg/kg, an increased pup loss was seen during the first 3 days postpartum, which was considered secondary to impaired maternal care due to maternal toxicity.
Labor and Delivery
Local anesthetics, including ropivacaine, rapidly cross the placenta, and when used for epidural block can cause varying degrees of maternal, fetal and neonatal toxicity (see CLINICAL PHARMACOLOGY and PHARMACOKINETICS). The incidence and degree of toxicity depend upon the procedure performed, the type and amount of drug used, and the technique of drug administration. Adverse reactions in the parturient, fetus and neonate involve alterations of the central nervous system, peripheral vascular tone and cardiac function.
Maternal hypotension has resulted from regional anesthesia with Naropin for obstetrical pain relief. Local anesthetics produce vasodilation by blocking sympathetic nerves. Elevating the patient's legs and positioning her on her left side will help prevent decreases in blood pressure. The fetal heart rate also should be monitored continuously, and electronic fetal monitoring is highly advisable. Epidural anesthesia has been reported to prolong the second stage of labor by removing the patient's reflex urge to bear down or by interfering with motor function. Spontaneous vertex delivery occurred more frequently in patients receiving Naropin than in those receiving bupivacaine.
Nursing Mothers
Some local anesthetic drugs are excreted in human milk and caution should be exercised when they are administered to a nursing woman. The excretion of ropivacaine or its metabolites in human milk has not been studied. Based on the milk/plasma concentration ratio in rats, the estimated daily dose to a pup will be about 4% of the dose given to the mother. Assuming that the milk/plasma concentration in humans is of the same order, the total Naropin dose to which the baby is exposed by breast-feeding is far lower than by exposure in utero in pregnant women at term (see PRECAUTIONS).
Pediatric Use
The safety and efficacy of Naropin in pediatric patients have not been established.
Geriatric Use
Of the 2,978 subjects that were administered Naropin Injection in 71 controlled and uncontrolled clinical studies, 803 patients (27%) were 65 years of age or older which includes 127 patients (4%) 75 years of age and over. Naropin Injection was found to be safe and effective in the patients in these studies. Clinical data in one published article indicate that differences in various pharmacodynamic measures were observed with increasing age. In one study, the upper level of analgesia increased with age, the maximum decrease of mean arterial pressure (MAP) declined with age during the first hour after epidural administration, and the intensity of motor blockade increased with age.
This drug and its metabolites are known to be excreted by the kidney, and the risk of toxic reactions to this drug may be greater in patients with impaired renal function. Elderly patients are more likely to have decreased hepatic, renal, or cardiac function, as well as concomitant disease. Therefore, care should be taken in dose selection, starting at the low end of the dosage range, and it may be useful to monitor renal function (see PHARMACOKINETICS, ELIMINATION).

Adverse Reactions

To report SUSPECTED ADVERSE REACTIONS, contact Fresenius Kabi USA, LLC at 1-800-551-7176 or FDA at 1-800-FDA-1088 or www.fda.gov/medwatch.
Reactions to ropivacaine are characteristic of those associated with other amide-type local anesthetics. A major cause of adverse reactions to this group of drugs may be associated with excessive plasma levels, which may be due to overdosage, unintentional intravascular injection or slow metabolic degradation.
The reported adverse events are derived from clinical studies conducted in the U.S. and other countries. The reference drug was usually bupivacaine. The studies used a variety of premedications, sedatives, and surgical procedures of varying length. A total of 3,988 patients have been exposed to Naropin at concentrations up to 1% in clinical trials. Each patient was counted once for each type of adverse event.
Incidence ≥5%
For the indications of epidural administration in surgery, cesarean section, postoperative pain management, peripheral nerve block, and local infiltration, the following treatment-emergent adverse events were reported with an incidence of ≥ 5% in all clinical studies (N=3988): hypotension (37%), nausea (24.8%), vomiting (11.6%), bradycardia (9.3%), fever (9.2%), pain (8%), postoperative complications (7.1%), anemia (6.1%), paresthesia (5.6%), headache (5.1%), pruritus (5.1%), and back pain (5%).
Incidence 1 to 5%
Urinary retention, dizziness, rigors, hypertension, tachycardia, anxiety, oliguria, hypoesthesia, chest pain, hypokalemia, dyspnea, cramps, and urinary tract infection.
Incidence in Controlled Clinical Trials
The reported adverse events are derived from controlled clinical studies with Naropin (concentrations ranged from 0.125% to 1% for Naropin and 0.25% to 0.75% for bupivacaine) in the U.S. and other countries involving 3,094 patients. TABLE 3A and 3B list adverse events (number and percentage) that occurred in at least 1% of Naropin-treated patients in these studies. The majority of patients receiving concentrations higher than 5 mg/mL (0.5%) were treated with Naropin.
Table 3A Adverse Events Reported in ≥1% of Adult Patients Receiving Regional or Local Anesthesia (Surgery, Labor, Cesarean Section, Postoperative Pain Management, Peripheral Nerve Block and Local Infiltration)

Table 3B Adverse Events Reported in ≥1% of Fetuses or Neonates of Mothers Who Received Regional Anesthesia (Cesarean Section and Labor Studies)

Incidence <1%

The following adverse events were reported during the Naropin clinical program in more than one patient (N=3988), occurred at an overall incidence of <1%, and were considered relevant:

Application Site Reactions - injection site pain
Cardiovascular System - vasovagal reaction, syncope, postural hypotension, non-specific ECG abnormalities
Female Reproductive - poor progression of labor, uterine atony
Gastrointestinal System - fecal incontinence, tenesmus, neonatal vomiting
General and Other Disorders - hypothermia, malaise, asthenia, accident and/or injury
Hearing and Vestibular - tinnitus, hearing abnormalities
Heart Rate and Rhythm - extrasystoles, non-specific arrhythmias, atrial fibrillation
Liver and Biliary System - jaundice
Metabolic Disorders - hypomagnesemia
Musculoskeletal System - myalgia
Myo/Endo/Pericardium - ST segment changes, myocardial infarction
Nervous System - tremor, Horner's syndrome, paresis, dyskinesia, neuropathy, vertigo, coma, convulsion, hypokinesia, hypotonia, ptosis, stupor
Psychiatric Disorders - agitation, confusion, somnolence, nervousness, amnesia, hallucination, emotional lability, insomnia, nightmares
Respiratory System - bronchospasm, coughing
Skin Disorders - rash, urticaria
Urinary System Disorders - urinary incontinence, micturition disorder
Vascular - deep vein thrombosis, phlebitis, pulmonary embolism
Vision - vision abnormalities
For the indication epidural anesthesia for surgery, the 15 most common adverse events were compared between different concentrations of Naropin and bupivacaine. TABLE 4 is based on data from trials in the U.S. and other countries where Naropin was administered as an epidural anesthetic for surgery.
Table 4 Common Events (Epidural Administration)

Using data from the same studies, the number (%) of patients experiencing hypotension is displayed by patient age, drug and concentration in TABLE 5. In TABLE 6, the adverse events for Naropin are broken down by gender.

Table 5 Effects of Age on Hypotension (Epidural Administration) Total N: Naropin = 760

Table 6 Most Common Adverse Events by Gender (Epidural Administration) Total N: Females = 405, Males = 355 Systemic Reactions

The most commonly encountered acute adverse experiences that demand immediate countermeasures are related to the central nervous system and the cardiovascular system. These adverse experiences are generally dose-related and due to high plasma levels that may result from overdosage, rapid absorption from the injection site, diminished tolerance or from unintentional intravascular injection of the local anesthetic solution. In addition to systemic dose-related toxicity, unintentional subarachnoid injection of drug during the intended performance of lumbar epidural block or nerve blocks near the vertebral column (especially in the head and neck region) may result in underventilation or apnea ("Total or High Spinal"). Also, hypotension due to loss of sympathetic tone and respiratory paralysis or underventilation due to cephalad extension of the motor level of anesthesia may occur. This may lead to secondary cardiac arrest if untreated. Factors influencing plasma protein binding, such as acidosis, systemic diseases that alter protein production or competition with other drugs for protein binding sites, may diminish individual tolerance.

Epidural administration of Naropin has, in some cases, as with other local anesthetics, been associated with transient increases in temperature to >38.5°C. This occurred more frequently at doses of Naropin > 16 mg/h.
Neurologic Reactions
These are characterized by excitation and/or depression. Restlessness, anxiety, dizziness, tinnitus, blurred vision or tremors may occur, possibly proceeding to convulsions. However, excitement may be transient or absent, with depression being the first manifestation of an adverse reaction. This may quickly be followed by drowsiness merging into unconsciousness and respiratory arrest. Other central nervous system effects may be nausea, vomiting, chills, and constriction of the pupils.
The incidence of convulsions associated with the use of local anesthetics varies with the route of administration and the total dose administered. In a survey of studies of epidural anesthesia, overt toxicity progressing to convulsions occurred in approximately 0.1% of local anesthetic administrations.
The incidence of adverse neurological reactions associated with the use of local anesthetics may be related to the total dose and concentration of local anesthetic administered and are also dependent upon the particular drug used, the route of administration, and the physical status of the patient. Many of these observations may be related to local anesthetic techniques, with or without a contribution from the drug. During lumbar epidural block, occasional unintentional penetration of the subarachnoid space by the catheter or needle may occur. Subsequent adverse effects may depend partially on the amount of drug administered intrathecally as well as the physiological and physical effects of a dural puncture. These observations may include spinal block of varying magnitude (including high or total spinal block), hypotension secondary to spinal block, urinary retention, loss of bladder and bowel control (fecal and urinary incontinence), and loss of perineal sensation and sexual function. Signs and symptoms of subarachnoid block typically start within 2 to 3 minutes of injection. Doses of 15 and 22.5 mg of Naropin resulted in sensory levels as high as T5 and T4, respectively. Analgesia started in the sacral dermatomes in 2 to 3 minutes and extended to the T10 level in 10 to 13 minutes and lasted for approximately 2 hours. Other neurological effects following unintentional subarachnoid administration during epidural anesthesia may include persistent anesthesia, paresthesia, weakness, paralysis of the lower extremities, and loss of sphincter control; all of which may have slow, incomplete or no recovery. Headache, septic meningitis, meningismus, slowing of labor, increased incidence of forceps delivery, or cranial nerve palsies due to traction on nerves from loss of cerebrospinal fluid have been reported (see DOSAGE AND ADMINISTRATION discussion of Lumbar Epidural Block). A high spinal is characterized by paralysis of the arms, loss of consciousness, respiratory paralysis and bradycardia.
Cardiovascular System Reactions
High doses or unintentional intravascular injection may lead to high plasma levels and related depression of the myocardium, decreased cardiac output, heart block, hypotension, bradycardia, ventricular arrhythmias, including ventricular tachycardia and ventricular fibrillation, and possibly cardiac arrest (see WARNINGS, PRECAUTIONS, and OVERDOSAGE).
Allergic Reactions
Allergic type reactions are rare and may occur as a result of sensitivity to the local anesthetic (see WARNINGS). These reactions are characterized by signs such as urticaria, pruritus, erythema, angioneurotic edema (including laryngeal edema), tachycardia, sneezing, nausea, vomiting, dizziness, syncope, excessive sweating, elevated temperature, and possibly, anaphylactoid symptomatology (including severe hypotension). Cross-sensitivity among members of the amide-type local anesthetic group has been reported. The usefulness of screening for sensitivity has not been definitively established.

Overdosage

Acute emergencies from local anesthetics are generally related to high plasma levels encountered, or large doses administered, during therapeutic use of local anesthetics or to unintended subarachnoid or intravascular injection of local anesthetic solution (see ADVERSE REACTIONS, WARNINGS, and PRECAUTIONS).

Management of Local Anesthetic Emergencies

Therapy with Naropin should be discontinued at the first sign of toxicity. No specific information is available for the treatment of toxicity with Naropin; therefore, treatment should be symptomatic and supportive. The first consideration is prevention, best accomplished by incremental injection of Naropin, careful and constant monitoring of cardiovascular and respiratory vital signs and the patient's state of consciousness after each local anesthetic and during continuous infusion. At the first sign of change in mental status, oxygen should be administered.

The first step in the management of systemic toxic reactions, as well as underventilation or apnea due to unintentional subarachnoid injection of drug solution, consists of immediate attention to the establishment and maintenance of a patent airway and effective assisted or controlled ventilation with 100% oxygen with a delivery system capable of permitting immediate positive airway pressure by mask. Circulation should be assisted as necessary. This may prevent convulsions if they have not already occurred.

If necessary, use drugs to control convulsions. Intravenous barbiturates, anticonvulsant agents, or muscle relaxants should only be administered by those familiar with their use. Immediately after the institution of these ventilatory measures, the adequacy of the circulation should be evaluated. Supportive treatment of circulatory depression may require administration of intravenous fluids, and, when appropriate, a vasopressor dictated by the clinical situation (such as ephedrine or epinephrine to enhance myocardial contractile force).

Should cardiac arrest occur, prolonged resuscitative efforts may be required to improve the probability of a successful outcome.

The mean dosages of ropivacaine producing seizures, after intravenous infusion in dogs, nonpregnant and pregnant sheep were 4.9, 6.1 and 5.9 mg/kg, respectively. These doses were associated with peak arterial total plasma concentrations of 11.4, 4.3 and 5 mcg/mL, respectively.

In human volunteers given intravenous Naropin, the mean (min-max) maximum tolerated total and free arterial plasma concentrations were 4.3 (3.4 to 5.3) and 0.6 (0.3 to 0.9) mcg/mL respectively, at which time moderate CNS symptoms (muscle twitching) were noted.

Clinical data from patients experiencing local anesthetic induced convulsions demonstrated rapid development of hypoxia, hypercarbia and acidosis within a minute of the onset of convulsions. These observations suggest that oxygen consumption and carbon dioxide production are greatly increased during local anesthetic convulsions and emphasize the importance of immediate and effective ventilation with oxygen which may avoid cardiac arrest.

If difficulty is encountered in the maintenance of a patent airway or if prolonged ventilatory support (assisted or controlled) is indicated, endotracheal intubation, employing drugs and techniques familiar to the clinician, may be indicated after initial administration of oxygen by mask.

The supine position is dangerous in pregnant women at term because of aortocaval compression by the gravid uterus. Therefore, during treatment of systemic toxicity, maternal hypotension or fetal bradycardia following regional block, the parturient should be maintained in the left lateral decubitus position if possible, or manual displacement of the uterus off the great vessels should be accomplished. Resuscitation of obstetrical patients may take longer than resuscitation of non-pregnant patients and closed-chest cardiac compression may be ineffective. Rapid delivery of the fetus may improve the response to resuscitative efforts.

DOSAGE AND ADMINISTRATION

The rapid injection of a large volume of local anesthetic solution should be avoided and fractional (incremental) doses should always be used. The smallest dose and concentration required to produce the desired result should be administered.
There have been adverse event reports of chondrolysis in patients receiving intra-articular infusions of local anesthetics following arthroscopic and other surgical procedures. Naropin is not approved for this use (see WARNINGS and DOSAGE AND ADMINISTRATION).

The dose of any local anesthetic administered varies with the anesthetic procedure, the area to be anesthetized, the vascularity of the tissues, the number of neuronal segments to be blocked, the depth of anesthesia and degree of muscle relaxation required, the duration of anesthesia desired, individual tolerance, and the physical condition of the patient. Patients in poor general condition due to aging or other compromising factors such as partial or complete heart conduction block, advanced liver disease or severe renal dysfunction require special attention although regional anesthesia is frequently indicated in these patients. To reduce the risk of potentially serious adverse reactions, attempts should be made to optimize the patient's condition before major blocks are performed, and the dosage should be adjusted accordingly.
Use an adequate test dose (3 to 5 mL of a short acting local anesthetic solution containing epinephrine) prior to induction of complete block. This test dose should be repeated if the patient is moved in such a fashion as to have displaced the epidural catheter. Allow adequate time for onset of anesthesia following administration of each test dose.
Parenteral drug products should be inspected visually for particulate matter and discoloration prior to administration, whenever solution and container permit. Solutions which are discolored or which contain particulate matter should not be administered.
The doses in the table are those considered to be necessary to produce a successful block and should be regarded as guidelines for use in adults. Individual variations in onset and duration occur. The figures reflect the expected average dose range needed. For other local anesthetic techniques standard current textbooks should be consulted.
When prolonged blocks are used, either through continuous infusion or through repeated bolus administration, the risks of reaching a toxic plasma concentration or inducing local neural injury must be considered. Experience to date indicates that a cumulative dose of up to 770 mg Naropin administered over 24 hours is well tolerated in adults when used for postoperative pain management: i.e., 2016 mg. Caution should be exercised when administering Naropin for prolonged periods of time, e.g., > 70 hours in debilitated patients.
For treatment of postoperative pain, the following technique can be recommended: If regional anesthesia was not used intraoperatively, then an initial epidural block with 5 to 7 mL Naropin is induced via an epidural catheter. Analgesia is maintained with an infusion of Naropin, 2 mg/mL (0.2%). Clinical studies have demonstrated that infusion rates of 6 to 14 mL (12 to 28 mg) per hour provide adequate analgesia with nonprogressive motor block. With this technique a significant reduction in the need for opioids was demonstrated. Clinical experience supports the use of Naropin epidural infusions for up to 72 hours.

How Supplied

Naropin® Single Dose Vials

Naropin® Single Dose Infusion Bottles

The solubility of ropivacaine is limited at pH above 6. Thus, care must be taken as precipitation may occur if Naropin is mixed with alkaline solutions.
Disinfecting agents containing heavy metals, which cause release of respective ions (mercury, zinc, copper, etc.) should not be used for skin or mucous membrane disinfection since they have been related to incidents of swelling and edema.
When chemical disinfection of the container surface is desired, either isopropyl alcohol (91%) or ethyl alcohol (70%) is recommended. It is recommended that chemical disinfection be accomplished by wiping the ampule or vial stopper thoroughly with cotton or gauze that has been moistened with the recommended alcohol just prior to use. When a container is required to have a sterile outside, a Sterile-Pak should be chosen. Glass containers may, as an alternative, be autoclaved once. Stability has been demonstrated using a targeted F 0 of 7 minutes at 121°C.
Solutions should be stored at 20º to 25°C (68º to 77°F) [see USP Controlled Room Temperature].
The container closure is not made with natural rubber latex.
These products are intended for single dose and are free from preservatives. Any solution remaining from an opened container should be discarded promptly. In addition, continuous infusion bottles should not be left in place for more than 24 hours.

Product repackaged by: Henry Schein, Inc., Bastian, VA 24314
From Original Manufacturer/Distributor's NDC and Unit of Sale | To Henry Schein Repackaged Product NDC and Unit of Sale | Total Strength/Total Volume (Concentration) per unit
NDC 63323-286-35 Unit of 25 | NDC 0404-9924-30 1 30 mL single dose vial in a bag (Vial bears NDC 63323-286-11) | 0.5% 150 mg per 30 mL (5 mg per mL)

NAROPIN is a trademark of Fresenius Kabi USA, LLC.
Lake Zurich, IL 60047
www.fresenius-kabi.com/us
Revised: June 2020